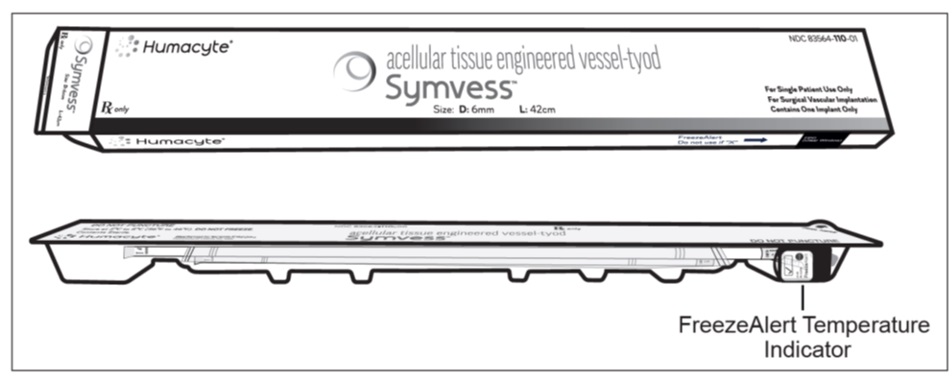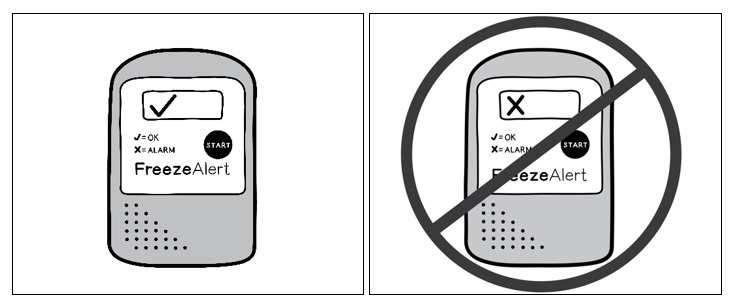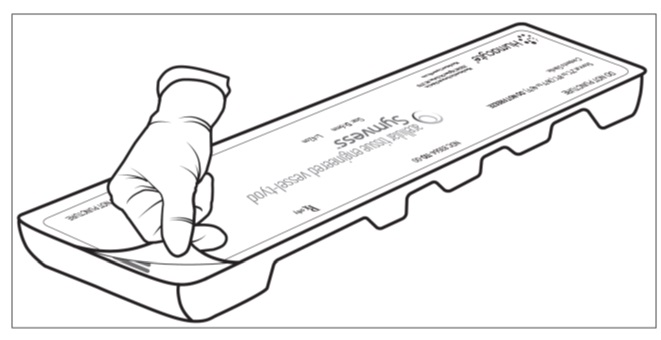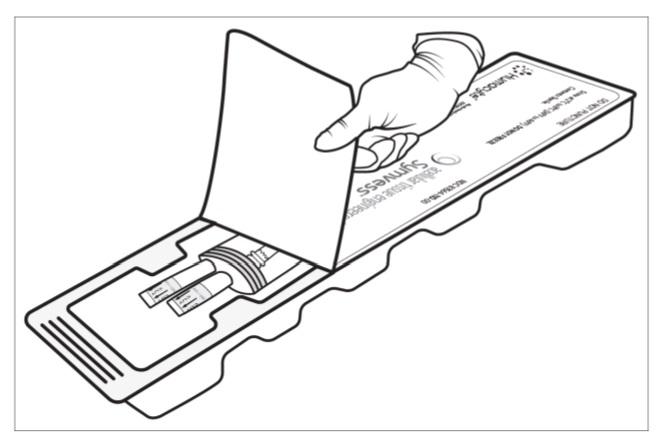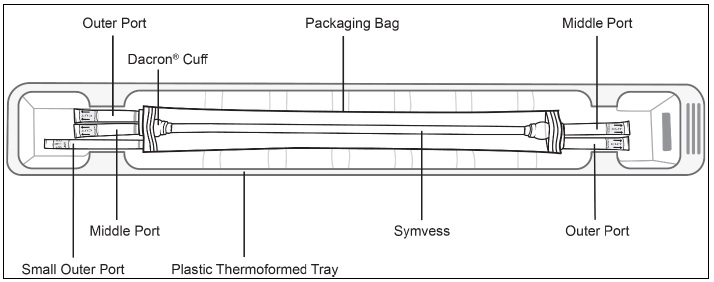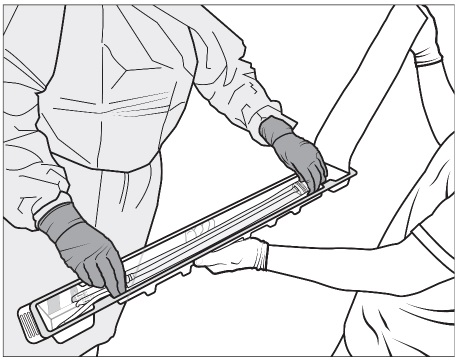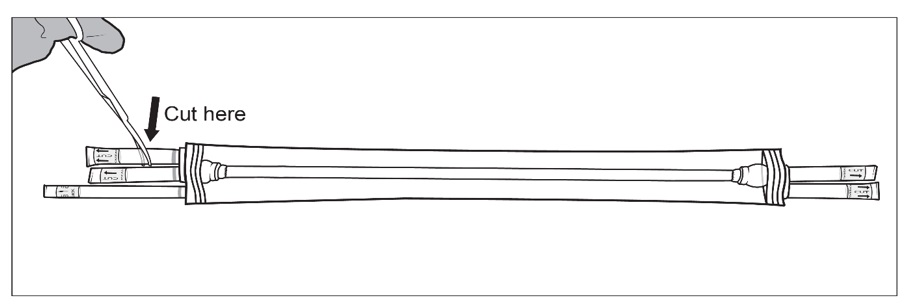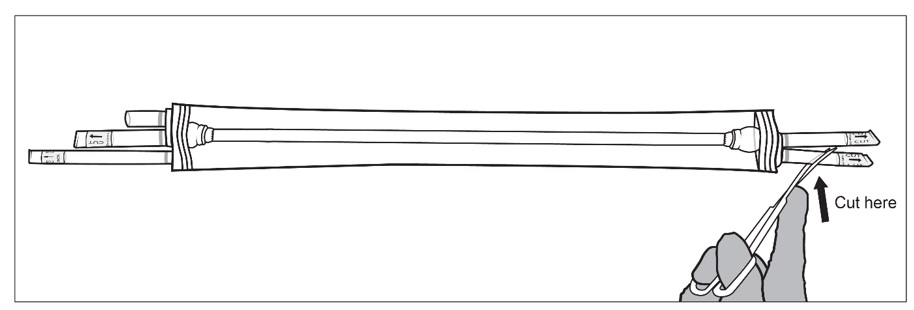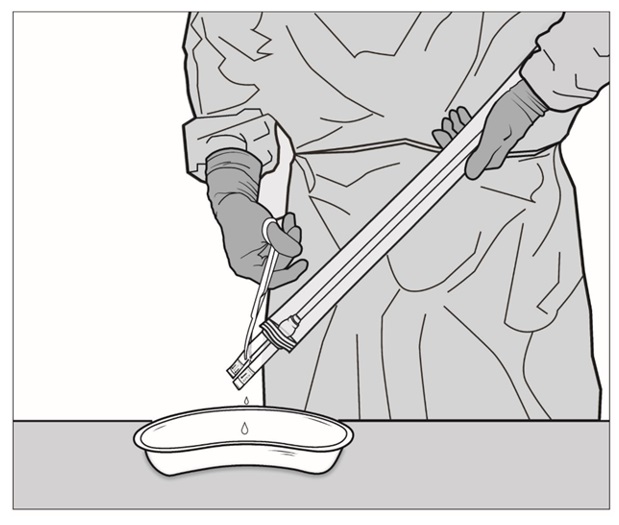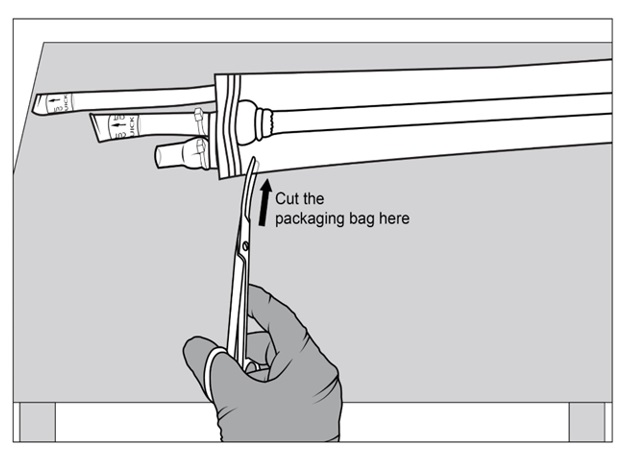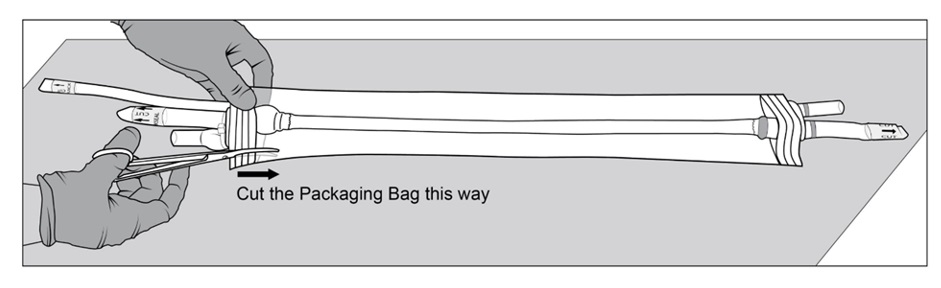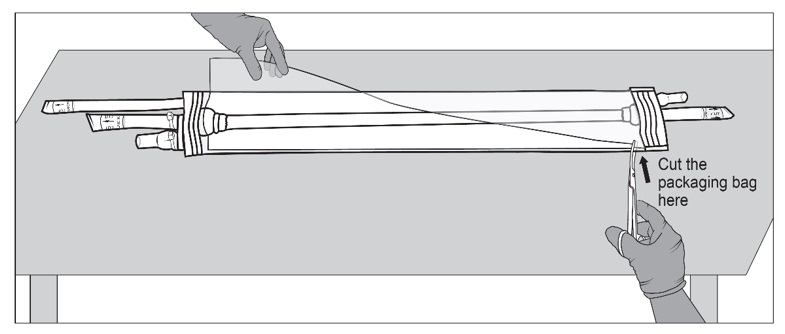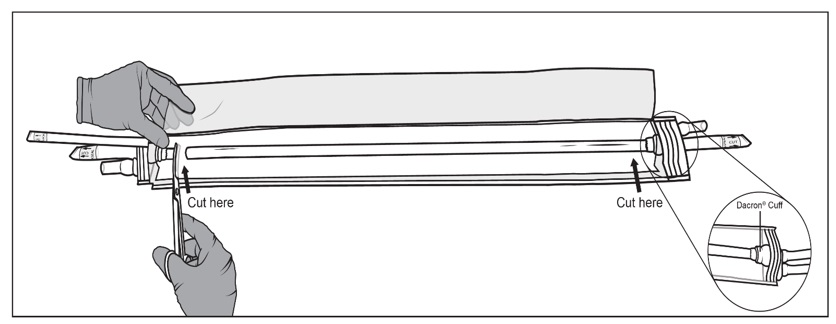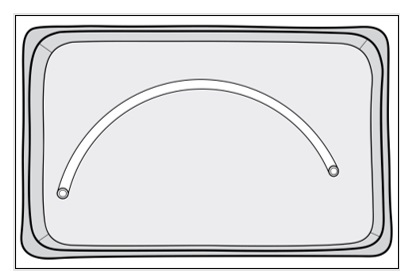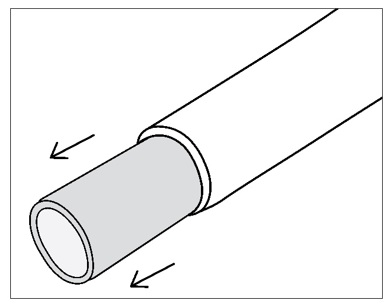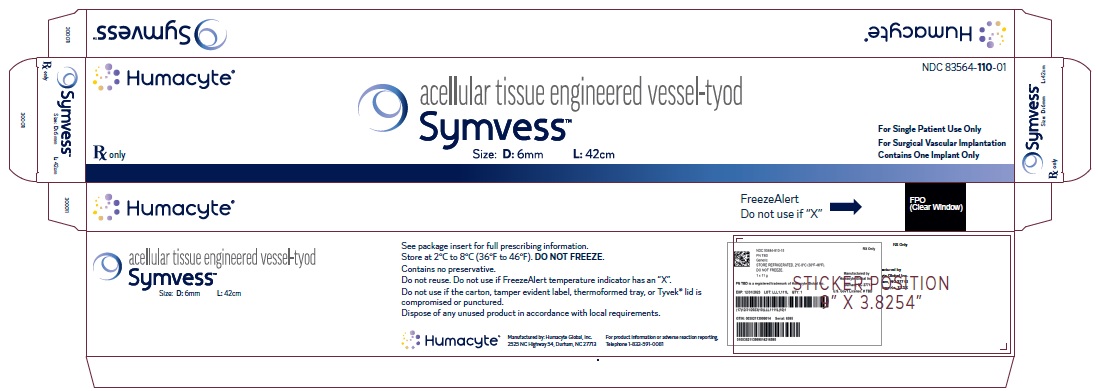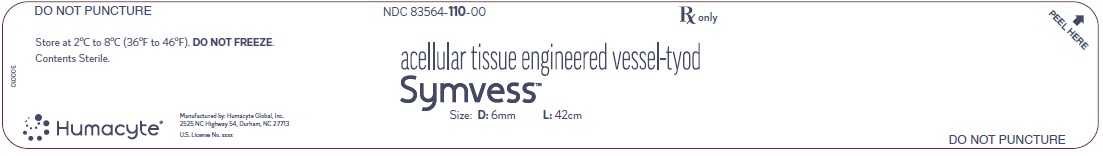 DRUG LABEL: Symvess
NDC: 83564-110 | Form: IMPLANT
Manufacturer: Humacyte Global, Inc.
Category: prescription | Type: HUMAN PRESCRIPTION DRUG LABEL
Date: 20251209

ACTIVE INGREDIENTS: ACELLULAR TISSUE ENGINEERED VESSEL 420 mm/1 1
INACTIVE INGREDIENTS: DPBS 1X, NO CALCIUM, NO MAGNESIUM

HIGHLIGHTS OF PRESCRIBING INFORMATION

These highlights do not include all the information needed to use SYMVESS safely and effectively. See full prescribing information for SYMVESS.
SYMVESS™ (acellular tissue engineered vessel-tyod), for surgical vascular implantation
Initial U.S. Approval: 2024

WARNING: GRAFT FAILURE

See full prescribing information for complete boxed warning.

- Loss of SYMVESS integrity due to mid-graft rupture or anastomotic failure can result in life threatening hemorrhage. (5.1, 5.2)

1 INDICATIONS AND USAGE

SYMVESS™ is an acellular tissue engineered vessel indicated for use in adults as a vascular conduit for extremity arterial injury when urgent revascularization is needed to avoid imminent limb loss, and autologous vein graft is not feasible. (1)

2 DOSAGE AND ADMINISTRATION

For surgical vascular implantation only.

- SYMVESS is administered by surgical implantation to replace the injured extremity artery. The anatomical location and length are decided upon at the discretion of the implanting surgeon and based on the appropriate preoperative clinical evaluation, vessel mapping and/or imaging. (2.1)
- SYMVESS may be trimmed to provide the length required for each vascular repair. Additionally, a single SYMVESS can be cut into different lengths and used to repair more than one injured extremity artery in the same patient. Each SYMVESS unit is for administration to a single patient only. (2.1)

3 DOSAGE FORMS AND STRENGTHS

SYMVESS is an acellular tissue engineered vessel composed of organized extracellular matrix (ECM) proteins. It has dimensions of 6 mm in inner diameter and 42 cm in length (approximately 40 cm of usable length). (3)

4 CONTRAINDICATIONS

DO NOT use SYMVESS in patients who have a medical condition that would preclude long-term antiplatelet therapy (such as aspirin or clopidogrel) after resolution of acute injuries.

5 WARNINGS AND PRECAUTIONS

- Graft Rupture. (5.1)
- Anastomotic Failure. (5.2)
- Thrombosis. (5.3)
- Transmission of Infectious Diseases (5.4)

6 ADVERSE REACTIONS

The most common adverse reactions (incidence ≥3%) were thrombosis, fever, pain, anastomotic stenosis, rupture or anastomotic failure, and infection. (6.1)

To report SUSPECTED ADVERSE REACTIONS, contact Humacyte Global, Inc. at 1-833-591-0081 or FDA at 1-800-FDA-1088 or www.fda.gov/medwatch.

FULL PRESCRIBING INFORMATION

WARNING: GRAFT FAILURE

- Loss of SYMVESS integrity due to mid-graft rupture or anastomotic failure can result in life threatening hemorrhage. [See Warnings and Precautions (5.1, 5.2)]

1 INDICATIONS AND USAGE

SYMVESS™ is an acellular tissue engineered vessel indicated for use in adults as a vascular conduit for extremity arterial injury when urgent revascularization is needed to avoid imminent limb loss, and autologous vein graft is not feasible.

2 DOSAGE AND ADMINISTRATION

2.1 Dosage

SYMVESS is administered by surgical implantation to replace the injured extremity artery. The anatomical location in the extremity and length required should be determined by the surgeon implanting the graft based on the appropriate pre-operative clinical evaluation, vessel mapping and/or imaging, and intra-operative considerations. SYMVESS is provided as follows: 6 mm in internal diameter and 42 cm in length. Once removed from packaging, its usable length is approximately 40 cm.

Each package (i.e., box containing Tyvek®-sealed tray) contains one SYMVESS unit for administration to a single patient only.

SYMVESS may be trimmed to provide the length required for the artery replacement. SYMVESS can be trimmed to replace more than one injured extremity artery in the same patient.

2.2 Handling of SYMVESS

Supplies:

The following supplies are not included in the carton, but may be needed for the handling of SYMVESS:

1) Sterile basin (as needed) – see Step 8 for details

2) Sheath tunneler (as needed) – see Section 2.3 and Step 3 for details

SYMVESS is to be handled in an appropriate surgical environment as follows:

Step 1: SYMVESS box contains a plastic thermoformed tray with a Tyvek® lid. Open the box and remove the plastic tray (Figure 1).

Figure 1: SYMVESS box and plastic tray

Step 2: After removing the tray from the box, check the FreezeAlert temperature indicator (Figure 2) attached to the side of the tray. If a check mark is displayed, SYMVESS has not been exposed to freezing temperatures and can be used. If an “X” is displayed, SYMVESS has been exposed to freezing temperatures and should NOT be used.

Figure 2: FreezeAlert Temperature indicator

Step 3: Two operators (one sterile operator and one non-sterile operator) are required to remove the sterile packaging bag containing SYMVESS from the plastic tray. Inspect the plastic tray to check for damage which can lead to loss in sterility of the SYMVESS. Do not open the tray for further use if the product is expired or has visible damage. If packaging is intact and within date of acceptable use, the non-sterile operator pulls back the Tyvek® lid by the corner tab to open the plastic tray containing the sterile packaging bag (Figure 3a and 3b). Take careful steps to avoid touching the sterile contents inside the tray (Figure 3c).

Figure 3a: Non-sterile operator pulls back the Tyvek® lid by the corner tab

Figure 3b: Non-sterile operator opens the plastic tray containing the sterile packaging bag

Figure 3c displays the components of SYMVESS within the plastic tray.

Figure 3c: SYMVESS with each component

Step 4: The non-sterile operator holds the bottom of the plastic tray with one hand and opens the Tyvek® lid with the other. The sterile operator removes the sterile packaging bag from the tray by grasping the ports (i.e., tubing) at the ends of the sterile packaging bag to remove the sterile packaging bag from the tray (Figure 4).

Place the sterile packaging bag on a sterile surface.

Figure 4: Sterile operator (grey gown and gloves; left) removes the packaging bag from plastic tray by grasping the ports (tubing) while non-sterile operator (white gloves; right) holds the plastic tray and opens the Tyvek® lid

Step 5: SYMVESS is suspended in sterile saline inside the packaging. The sterile operator cuts one or both of the outer ports on both ends of the packaging using sterile surgical scissors and drains the sterile saline solution contained within the packaging bag (Figure 5a, 5b and 5c).

NOTE: If the middle ports or the small outer port are accidentally cut, there is no need for concern.

Figure 5a, 5b and 5c: Sterile operator cuts both outer ports one at a time to drain saline solution using surgical scissors

Step 6: Once the saline solution has been drained, place the packaging bag back on a sterile surface. Using sterile surgical scissors or scalpel blade, cut a small slit on the edge of the packaging bag (Figure 6a), then make a second cut along the length of the packaging bag (Figure 6b). Be careful not to cut SYMVESS. If SYMVESS is accidentally nicked or cut during removal from the packaging bag, discard the damaged SYMVESS, and use a new SYMVESS. Make another cut on the other end of the packaging bag to allow for full exposure of SYMVESS (Figure 6c).

Figure 6a, 6b and 6c: Sterile operator cuts the packaging bag using surgical scissors to reveal SYMVESS

Step 7: Holding back the flaps of the open packaging bag, cut SYMVESS 1 cm from the Dacron® cuffs (below the blue sutures) to free it from the packaging bag (Figure 7). Approximately 40 cm in length of SYMVESS should be available for use.

Figure 7: Sterile operator cuts SYMVESS 1 cm from the Dacron® cuff using surgical scissors

Step 8: Use sterile gloves or atraumatic instruments when handling SYMVESS. SYMVESS is ready for immediate implantation OR should be kept immersed in a basin of sterile saline solution at room temperature while the patient is being prepared for surgical implantation (Figure 8). SYMVESS may be immersed in sterile saline solution for up to eight hours during surgical preparation for implantation. IF SYMVESS DRIES OUT, IT IS NOT USABLE AND MUST BE DISCARDED.

Figure 8: Store SYMVESS in a basin of sterile saline solution

Step 9: SYMVESS contains a clear silicone tube within the lumen. The silicone tube provides structural support to prevent kinking and twisting of SYMVESS when tunneling. The silicone tube can be left in place during any tunneling procedure but should be removed before making an anastomosis. To remove the inner silicone tube, gently grasp the end of SYMVESS and slide SYMVESS down to reveal the inner silicone tube, which can then be pulled out (Figure 9).

2.3 Administration

Surgically implant SYMVESS under appropriate aseptic conditions.

Follow the steps below for implantation of SYMVESS:

1. When handling SYMVESS, avoid using excessive force, which may lead to SYMVESS damage.
2. To avoid damage or contamination, always use sterile gloves and atraumatic instruments when handling SYMVESS. Always protect SYMVESS from damage by heavy or sharp instruments.
3. When necessary, a SHEATH TUNNELER may be used to safely deliver SYMVESS through subcutaneous or other tissues. Create a tissue tunnel that closely matches SYMVESS diameter (6 mm tunneller is recommended, but 8 mm tunneller is acceptable). A KELLY-WICK OR NON-SHEATHED TUNNELLER IS NOT RECOMMENDED FOR USE WITH SYMVESS. During the tunneling process, ensure that SYMVESS does not kink or twist within the tunnel. A twisted or kinked vessel will result in compromised flow and performance, thereby increasing the risk of thrombosis and failure.
4. It is recommended to keep the inner silicone tube in place within SYMVESS until any tunneling process is complete. Lubricate the lumen of the tunneller sheath with saline solution and then gently push SYMVESS with the silicone tube through the sheath (alternatively SYMVESS can be grasped by or secured to the inner sheath rod and pulled through the sheath). After the tunneling sheath is removed, the inner silicone tube is removed from SYMVESS.
  THE INNER SILICONE TUBE MUST BE REMOVED BEFORE CREATING AN ANASTOMOSIS (FIGURE 9)
  Figure 9: Remove the inner silicone tube within the lumen of SYMVESS BEFORE creating an anastomosis.
5. Following standard surgical procedures, the appropriate length to use for SYMVESS must be carefully determined. SYMVESS DOES NOT ELONGATE UNDER PRESSURE. Since SYMVESS does not elongate, the length must allow SYMVESS to adequately reach both anastomoses. SYMVESS should either be tunneled or held at the site of implantation so that the length to adequately reach both anastomoses is clear. The patient’s body size and posture, and the range of the motions likely to be encountered around the anatomical region of the implantation should be considered when determining length. Choosing the appropriate length of SYMVESS may prevent kinking, twisting, or damaging SYMVESS after implantation.
6. Failure to carefully cut SYMVESS may cause damage and result in failure at the anastomosis site or reduced suture retention strength. Cut SYMVESS with sharp vascular scissors as one would trim a human blood vessel prior to implantation. SYMVESS can be held with atraumatic instruments or sterile gloves while cutting with vascular scissors.
7. The anastomosis must be precise, and with meticulous attention to detail. SYMVESS may be anastomosed end-to-end or end-to-side with the patient’s vessels. An end-to-side anastomosis may accommodate size discrepancies between the host vessel and SYMVESS. Use of an appropriate anastomotic angle may minimize stresses upon SYMVESS which may reduce kinking and/or mechanical disruptions of SYMVESS, recipient or donor vessel, and/or suture lines.
8. Use of non-crushing vascular (atraumatic) clamp is recommended on SYMVESS to avoid mechanical damage or disruption to SYMVESS. AVOID REPEATED, LOCALIZED CLAMPING OR EXCESSIVE CLAMPING ON ANY SECTION OF SYMVESS.
9. Use only 5-0 or 6-0 non-absorbable, monofilament suture with size selected based on the nature of the anastomosis. Use of a suture size larger in diameter than 5-0 or smaller in diameter than 6-0 for anastomosis creation with SYMVESS may reduce suture retention.
10. A suture bite depth of 2.0-2.5mm is recommended to ensure suture retention.
11. Flush static blood from the lumen of SYMVESS while completing the second anastomosis. Failure to do so may result in thrombosis of the vessel.
12. Undue anastomotic bleeding may occur if gaps are present between SYMVESS and the host vessel. Use appropriate suture placement and avoid undue tension on the suture line. Topical hemostatic agents may be used to minimize anastomotic bleeding if desired, therefore, the use of these agents will be at the surgeon’s discretion.
13. Inspect the operative site carefully prior to closure. Ensure that SYMVESS is covered by healthy muscle and/or soft tissue. Ensure that there are no twists, kinks, redundancy, before and during the tissue closure portion of the case. It may be necessary to clear or release tissue to avoid SYMVESS impingement.
14. At the conclusion of the operation, inspect the circulation to ensure that perfusion to the distal vascular bed has not been compromised and assess for risk of compartment syndrome following revascularization.
15. Surgical interventions are permissible and up to the surgeon’s discretion. PERCUTANEOUS INTERVENTIONS SHOULD ONLY USE BALLOONS THAT DO NOT EXCEED 6MM IN DIAMETER. Larger diameter balloons used for angioplasty or thrombectomy procedures may result in tearing of the SYMVESS wall or development of pseudoaneurysm. Mechanical thrombectomy devices other than balloons have not been studied with SYMVESS in the trauma setting and therefore are not recommended.

3 DOSAGE FORMS AND STRENGTHS

SYMVESS is an acellular tissue engineered vessel composed of organized extracellular matrix (ECM) proteins. SYMVESS is implanted using standard surgical techniques as a vascular construct to replace a patient’s damaged extremity artery after injury. SYMVESS has dimensions of 6 mm in inner diameter and 42 cm in length (approximately 40 cm of usable length). Since the length of SYMVESS to be implanted is dependent on the surgical needs, it is cut to length by the surgeon in the operating room [see Administration (2.3 steps 5 and 6)].

4 CONTRAINDICATIONS

DO NOT use SYMVESS in patients who have a medical condition that would preclude long-term antiplatelet therapy (such as aspirin or clopidogrel) after resolution of acute injuries.

5 WARNINGS AND PRECAUTIONS

5.1 Graft Rupture

Vascular graft rupture has occurred in patients treated with SYMVESS [see Clinical Trials Experience (6.1)]. Advise patients that arterial bleeding can be life-threatening and to seek emergent medical evaluation for any signs or symptoms of graft rupture such as bleeding, pain and swelling in the extremity, or signs of extremity ischemia.

Follow appropriate procedures for handling and administering SYMVESS [see Dosage and Administration (2)].

5.2 Anastomotic Failure

Anastomotic failure has occurred in patients treated with SYMVESS [see Clinical Trials Experience (6.1)]. In clinical studies of SYMVESS, anastomotic failure occurred within the first 36 days post-implantation.

Monitor patients for signs of anastomotic failure such as pain and swelling at the surgical site, decreasing hemoglobin or other signs and symptoms of bleeding. Advise patients to seek urgent medical evaluation if they have any signs or symptoms that may be indicative of anastomotic failure such as bleeding, swelling or worsening pain at the surgical site or changes in color of overlying skin.

Follow appropriate procedures for handling and administering SYMVESS [see Dosage and Administration (2)].

5.3 Thrombosis

Thrombosis has occurred in patients treated with SYMVESS [see Clinical Trials Experience (6.1)]. In clinical trials of SYMVESS, patients received antiplatelet therapy following implantation of SYMVESS to reduce the risk of thrombosis. The risk of thrombosis may increase in patients who discontinue antiplatelet therapy.

Anti-platelet therapy is recommended following treatment with SYMVESS.

5.4 Transmission of Infectious Diseases

SYMVESS is manufactured using cells and reagents that may transmit infectious diseases or infectious agents. The cells used in the manufacture of SYMVESS are derived from a donor who met the donor eligibility requirements for transmissible infectious diseases which includes screening and testing of risks associated with human immunodeficiency virus 1 (HIV-1), human immunodeficiency virus 2 (HIV-2), hepatitis B virus (HBV), hepatitis C virus (HCV), and syphilis (Treponema pallidum). The cell banks are tested negative for human and animal viruses, retroviruses, bacteria, fungi, yeast, and mycoplasma. While all animal-derived reagents are tested for animal viruses, bacteria, fungi, and mycoplasma before use, these measures do not eliminate the risk of transmitting these or other transmissible infectious diseases and disease agents. Fetal bovine serum is sourced to minimize the risk of transmitting a prion protein that causes bovine spongiform encephalopathy and the cause of a rare fatal condition in humans called variant Creutzfeldt-Jakob disease. No transmissible agent infections have been reported during clinical testing.

6 ADVERSE REACTIONS

6.1 Clinical Trials Experience

Because clinical trials are conducted under widely varying conditions, adverse reaction rates observed in the clinical trials of a product cannot be directly compared to adverse reaction rates in clinical trials of other products, and they may not reflect the rates observed in real-world clinical practice.

The safety data described in this section reflect exposure to SYMVESS in one single arm, open-label study in patients requiring vascular replacement or reconstruction for life or limb threatening vascular trauma, Study 1 (CLN-PRO-V005; NCT03005418). A total of 54 adults received extremity implantation of SYMVESS as a vascular conduit.

The patient population ranged in age from 18 to 72 years (mean age 33 years). Each patient received a SYMVESS implant ranging in length from 1 to 35 cm (mean length 10.1 cm). The most frequently occurring adverse reactions are shown in Table 1.

Table 1 Adverse Reactions Occurring with a Frequency of ≥3% in Study 1
Adverse Reaction [Adverse Reaction Frequency based on up to 3 years follow-up data [median 191 days (range 1-1134 days)]] | Extremity Patients (%) [Extremity patients are with arterial repair in upper or lower limbs] (n=54)
Vascular graft thrombosis | 15 (28%)
Pyrexia (fever) | 9 (17%)
Pain | 8 (15%)
Anastomotic stenosis | 5 (9%)
Vascular graft rupture or anastomotic failure | 4 (7%)
Vascular graft infection | 3 (6%)

Long term follow-up of up to 36 months in Study 1 is ongoing. At the data cut-off date, 7 out of 54 patients in the extremity group have completed the study (i.e., completed 36 months of follow-up).

The safety of SYMVESS beyond 36 months was not evaluated in the clinical studies for this indication.

8 USE IN SPECIFIC POPULATIONS

8.1 Pregnancy

Risk Summary

The limited clinical data that are available with SYMVESS use in pregnant women are insufficient to inform a drug-associated risk. No animal reproductive and developmental toxicity studies have been conducted with SYMVESS to assess whether it can cause harm to the mother or fetus when administered to a pregnant woman.

In the U.S. general population, the estimated background risk of major birth defects and miscarriage in clinically recognized pregnancies is 2% to 4% and 15% to 20%, respectively.

8.2 Lactation

Risk Summary

There is no information regarding the transmission of antibodies or any components of SYMVESS in human milk, the effects on the breast-fed infant, or the effects on milk production. The developmental and health benefits of breastfeeding should be considered along with the mother’s clinical need for SYMVESS and any potential adverse effects on the breastfed infant from SYMVESS or from the underlying maternal condition.

8.4 Pediatric Use

The safety and effectiveness of SYMVESS in pediatric patients (0 to 17 years old) have not been established.

8.5 Geriatric Use

Two (2) patients out of the 54 Extremity Group implanted with SYMVESS as a conduit in Study 1 were aged ≥65 years. The number of patients aged ≥65 years was not sufficient to determine whether they responded differently than younger patients to SYMVESS.

11 DESCRIPTION

SYMVESS is a sterile, acellular tissue engineered vessel composed of human extracellular matrix (ECM) proteins typically found in human blood vessels. SYMVESS is 6 mm in internal diameter and 42 cm in length (approximately 40 cm of usable length).

SYMVESS is manufactured using a tissue engineering process. Human vascular smooth muscle cells that are derived from human aortic tissue deemed suitable for transplant are banked, expanded, and seeded onto a tubular mesh scaffold. The cell-seeded scaffold is cultured in a biomimetic bioreactor system to generate an intermediate tubular construct containing vascular smooth muscle cells and the extracellular matrix the cells deposited. A final decellularization process removes the human cellular and genetic material while maintaining the extracellular matrix structure and mechanical and biological activity.

SYMVESS manufacture includes use of reagents derived from human and animal materials. Human male AB serum and fetal bovine serum (FBS) are used in the manufacturing process for the cultivation and expansion of the vascular smooth muscle cells.

SYMVESS is fixed inside the packaging bag between the endcaps with a supporting silicone tube and is immersed in sterile phosphate buffered saline solution.

12 CLINICAL PHARMACOLOGY

12.1 Mechanism of Action

SYMVESS is an acellular tissue engineered vessel composed of human extracellular matrix (ECM) that exhibits mechanical and biological activity. Product testing results have shown that SYMVESS can withstand the forces associated with the arterial blood flow and suturing during implantation. Product testing results have also demonstrated that SYMVESS ECM can support cell binding and proliferation. However, the exact mechanism of action has not been established.

12.2 Pharmacodynamics

The pharmacodynamic effects of SYMVESS are not known.

12.3 Pharmacokinetics

The pharmacokinetic effects of SYMVESS are not known.

13 NONCLINICAL TOXICOLOGY

13.1 Carcinogenesis, Mutagenesis, Impairment of Fertility

Conventional carcinogenicity and reproductive and developmental toxicity studies have not been conducted. Results from in vitro studies including a bacterial reverse mutation assay, L-929 mouse fibroblast assay, and human lymphocyte chromosomal aberration assay demonstrated that SYMVESS material is non-mutagenic.

14 CLINICAL STUDIES

The efficacy and safety of SYMVESS as a vascular conduit for extremity arterial trauma repair was evaluated in a subset of patients enrolled in Study 1 (CLN-PRO-V005; NCT03005418) who had extremity arterial injuries that were life or limb threatening, and in Study 2 (CLN-PRO-V017; NCT05873959) as described below.

Study 1

This is a prospective, single arm, multicenter study conducted to evaluate safety and efficacy of SYMVESS for vascular replacement in patients with life or limb threatening vascular trauma. For inclusion in the study, patients must have been adults with an arterial defect length less than or equal to 38 cm that must be appropriately size matched to the 6 mm SYMVESS inner diameter. The study excluded patients with a mangled extremity severity score (MESS) greater than or equal to 7 or an abbreviated injury scale (AIS) greater than 5 from study participation.

The primary efficacy outcome measure was the rate of primary vascular graft patency at Day 30 in patients with extremity arterial injury assessed using duplex ultrasound or equivalent (i.e., CTA, MRI). Additional efficacy outcome measures included secondary patency at Day 30, conduit infection within first 30 days and limb salvage at Day 30 post implantation.

A total of 54 patients with a median age of 30 years (range 18 to 72 years) received SYMVESS as a conduit for extremity arterial trauma repair. Twenty-six patients (48%) were Black or African American and 23 patients (43%) were White and five patients (9%) were classified as other. Forty patients (74%) were male. The distribution of type of trauma was 31 (57%) penetrating trauma and 23 (43%) blunt trauma. The Day 30 efficacy outcomes are summarized in Table 2.

Table 2 Outcomes for the extremity group of Study 1 at Day 30 (N = 54) [Nine patients not available for Day 30 assessment were imputed as failures for patency and limb salvage estimation]
Endpoint | n=54 | % (95% CI)
Primary Patency | 36 | 66.7% (53.4%, 77.8%)
Secondary Patency | 39 | 72.2% (59.1%, 82.4%)
Vascular Graft Infections | 1 | 1.9% (0.3%, 9.8%)
Limb Salvage | 41 | 75.9% (63.1%, 85.4%)

Nine (9) patients had confirmed loss of primary patency over the first thirty days, of which, six patients had also lost secondary patency. Of the thirteen patients not available for Day 30 evaluation, four patients had confirmed loss of patency (one SYMVESS infection and removal and subsequent amputation, three patients with thrombosis leading to SYMVESS removal in two patients and the thrombosed SYMVESS left in place with good collateral circulation in the third patient). The remaining nine patients who were not evaluable for patency assessment were due to loss to follow-up (1 patient), amputation (4 patients), or death (4 patients).

Seven (7) out of 54 (13%) patients completed 36-month follow-up with a further 10 (19%) patients ongoing at the time of data cutoff for the 120-day safety report. Reasons for early discontinuation from the study included: loss to follow-up (n=13, 24%), SYMVESS abandonment (n=10, 19%), death (n=6, 11%), limb amputation (n=6, 11%), and withdrawal of consent (n=2, 4%). Patient follow-up ranged from 1-1134 days (median = 191 days) with 41 (76%) patients who were followed for at least 30 days, 30 (56%) patients were followed for at least six months and 17 (32%) patients were followed for at least one year.

Study 2

This is an observational study consisting of a retrospective analysis of point of care clinical data in patients who received SYMVESS in Ukraine. The study included patients who received SYMVESS to repair traumatic life- or limb-threatening vascular extremity injuries. Patients with a damaged upper or lower limb artery less than or equal to 38 cm and appropriately size matched to the 6 mm SYMVESS inner diameter were included. The study excluded patients with a mangled extremity severity score (MESS) of > 7 or an abbreviated injury scale (AIS) > 5.

The primary efficacy outcome measure was the rate of primary vascular graft patency at Day 30 using duplex ultrasound. Additional efficacy outcome measures included secondary patency at Day 30, conduit infection within first 30 days and limb salvage at Day 30 post implantation. Among the 16 patients in the study, the median age was 31 years (range 22 to 54 years). All patients were White and male. The distribution of type of trauma was 87.5% penetrating and 12.5% blunt trauma. The median follow-up duration in Study 2 was 366 days (range 13-573 days). SYMVESS implanted length ranged from 3.5 to 40 cm (mean = 18.3 cm). All 16 (100%) patients were evaluable for 30-day patency. Fifteen patients (94%) retained primary and secondary patency at Day 30. One (1) patient had SYMVESS replaced on Day 13 due to recurrent bleeding following rupture of conduit. Infection rate was 0% at Day 30. Limb salvage rate was 100% at Day 30.

16 HOW SUPPLIED/STORAGE AND HANDLING

16.1 How Supplied

SYMVESS is for single patient use only and is supplied in a sealed sterile packaging bag. The packaging bag is contained within a plastic thermoformed tray sealed with a Tyvek® lid, the contents of which are sterile. The sealed plastic thermoformed tray (NDC 83564-110-00) is contained within a non-sterile carton (NDC 83564-110-01).

SYMVESS is fixed inside the packaging bag between the endcaps with a supporting silicone tube and is immersed in sterile phosphate buffered saline solution. SYMVESS, the saline solution, and the outer surface of the packaging bag are sterile.

SYMVESS is shipped in an insulated shipping box (2ºC to 8ºC).

16.2 Storage and Handling

Store SYMVESS at 2ºC to 8ºC (36ºF to 46ºF).
Use SYMVESS prior to the expiration date printed on the carton.
Do not freeze.

A FreezeAlert temperature indicator is attached to the exterior of each thermoformed tray that contains a SYMVESS. Prior to preparing SYMVESS for a procedure, check the FreezeAlert indicator. A check mark indicates SYMVESS has not been exposed to freezing temperatures and can be used. An “X” displayed on the indicator signifies that SYMVESS has been exposed to freezing temperatures and should NOT be used [see Handling of SYMVESS (2.2)].

DO NOT use SYMVESS if:

- carton has been damaged
- Tyvek® lid is punctured or detached
- thermoformed tray is punctured or compromised
- there is evidence of fluid leakage from the packaging bag
- FreezeAlert temperature indicator has an “X”

Dispose of unused SYMVESS and packaging bag using established clinical facility procedures in accordance with local regulatory requirements.

Contact Customer Care at 1-833-591-0081 for further instructions or questions.

17 PATIENT COUNSELING INFORMATION

Counsel the patient on the following:

- Graft Rupture
  Inform patients that bleeding can occur from the graft site and that subsequent intervention, explant, or additional procedures may be required after initial repair. Advise patients to seek urgent medical evaluation if they develop any bleeding from the surgical site, or have any signs or symptoms that would indicate failure of the graft such as worsening pain, loss of limb function or change in color of overlying skin. [see Warnings and Precautions (5.1)].
- Anastomotic Failure
  Inform patients that in certain situations, bleeding can occur at the graft anastomosis site and that subsequent intervention, explant, or additional procedures may be required to repair this. Advise patients to seek urgent medical evaluation if they have any signs or symptoms that may be indicative of anastomotic failure such as bleeding, swelling or worsening pain at the surgical site or changes in color of overlying skin. [see Warnings and Precautions (5.2)].
- Thrombosis
  Inform patients that in certain situations, thrombosis can occur after SYMVESS implantation. At the surgeon's discretion, consider use of antiplatelet therapy following implantation of SYMVESS to reduce the risk of thrombosis. The risk of thrombosis may increase in patients who discontinue antiplatelet therapy. Advise patients to seek urgent medical evaluation if they have any signs or symptoms that may be indicative of thrombosis including worsening pain at the surgical site, swelling, changes of color of the overlying skin, or warm skin around the painful area. [see Warnings and Precautions (5.3)].
- Transmission of Infectious Diseases
  Inform patients of the possible risk of transmission of infectious diseases with SYMVESS. [see Warnings and Precautions (5.4)].

Manufactured by:
Humacyte Global, Inc.
2525 E. NC Highway 54
Durham, NC 27713
USA

SYMVESS™ is a trademark of Humacyte Global, Inc.

PRINCIPAL DISPLAY PANEL

NDC 83564-110-01

Humacyte®

acellular tissue engineered vessel-tyod

Symvess™
Size: D: 6mm L: 42cm

Rx only

For Single Patient Use Only
For Surgical Vascular Implantation
Contains One Implant Only

PRINCIPAL DISPLAY PANEL

DO NOT PUNCTURE

NDC 83564-110-00

Rx only

PEEL HERE

Store at 2ºC to 8ºC (36ºF to 46ºF). DO NOT FREEZE.

Contents Sterile.

acellular tissue engineered vessel-tyod

Symvess™
Size: D: 6mm L: 42cm

Humacyte®

Manufactured by: Humacyte Global, Inc.
2525 NC Highway 54, Durham, NC 27713

U.S. License No. 2336

DO NOT PUNCTURE